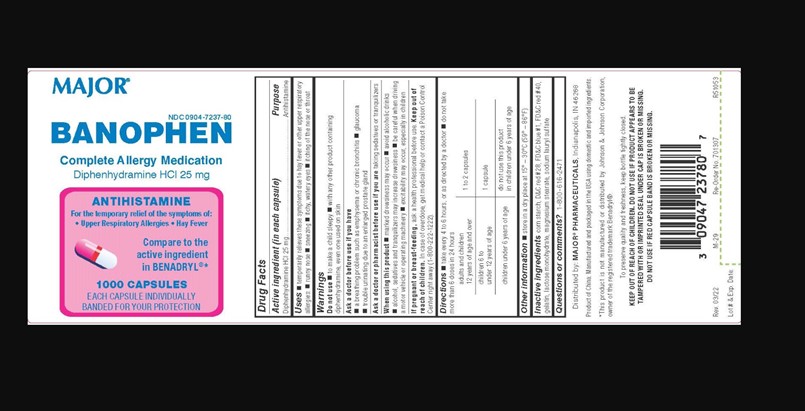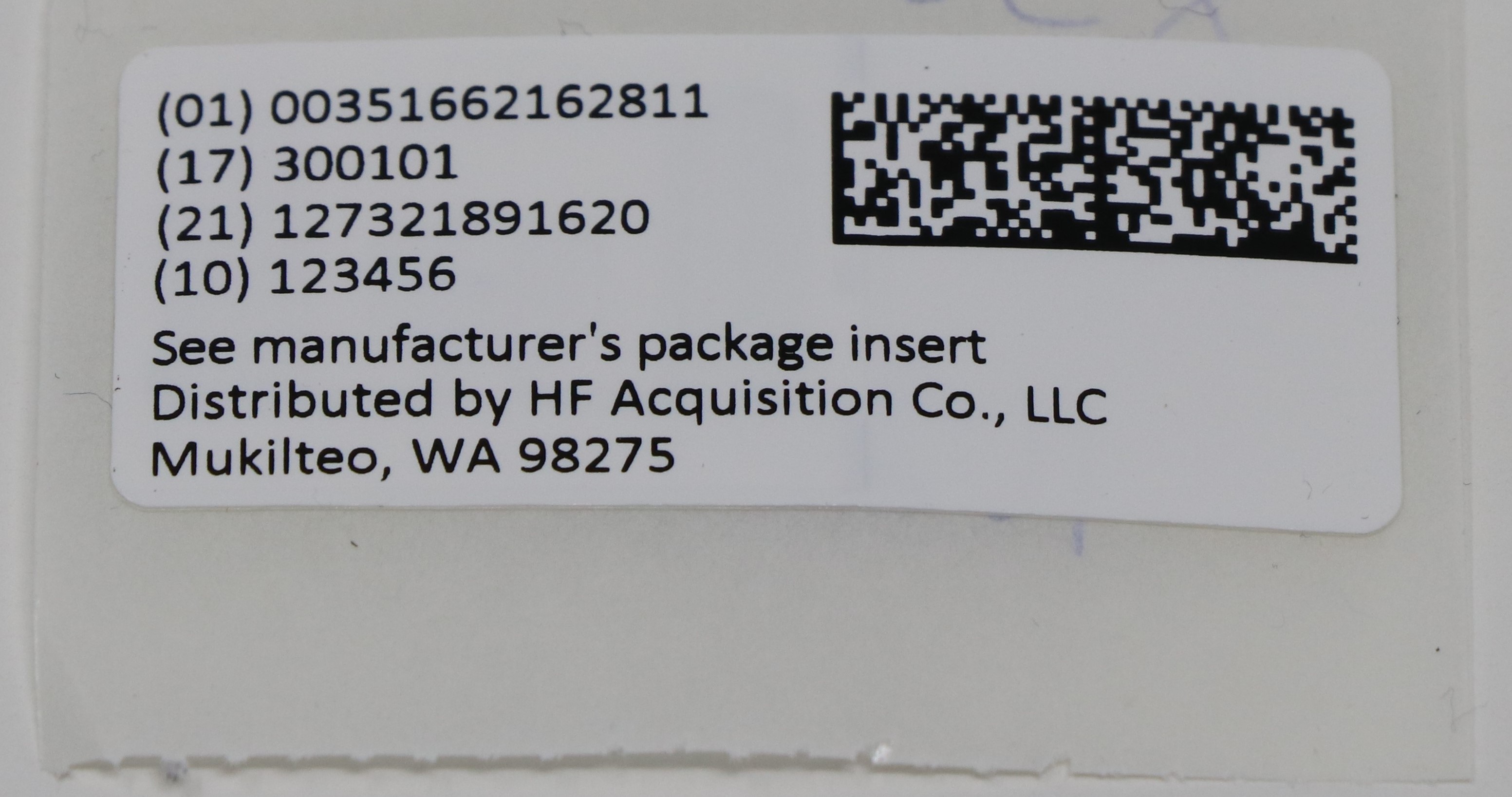 DRUG LABEL: Diphenhydramine HYDROCHLORIDE
NDC: 51662-1628 | Form: CAPSULE
Manufacturer: HF Acquisition Co LLC, DBA HealthFirst
Category: otc | Type: HUMAN OTC DRUG LABEL
Date: 20241021

ACTIVE INGREDIENTS: DIPHENHYDRAMINE HYDROCHLORIDE 25 mg/1 1
INACTIVE INGREDIENTS: GELATIN; FD&C BLUE NO. 1; SODIUM LAURYL SULFATE; STARCH, CORN; D&C RED NO. 28; FD&C RED NO. 40; MAGNESIUM STEARATE; LACTOSE MONOHYDRATE

DRUG FACTS

Active ingredient (in each capsule)
Diphenhydramine HCl 25 mg

Purpose
Antihistamine

USES

 temporarily relieves these symptoms due to hay fever or other upper respiratory allergies:  runny nose  sneezing  itchy, watery eyes  itching of the nose or throat

WARNINGS

 to make a child sleepy

 with any other product containing diphenhydramine, even one used on skin

Ask a doctor before use if you have
 a breathing problem such as emphysema or chronic bronchitis

 glaucoma
 trouble urinating due to an enlarged prostate gland

Ask a doctor or pharmacist before use if you are taking sedatives or tranquilizers

When using this product

 marked drowsiness may occur

 avoid alcoholic drinks
 alcohol, sedatives and tranquilizers may increase drowsiness

 be careful when driving a motor vehicle or operating machinery

 excitability may occur, especially in children

If pregnant or breast-feeding, ask a health professional before use.

Keep out of reach of children.

In case of overdose, get medical help or contact a Poison Control Center right away (1-800-222-1222).

DIRECTIONS

 take every 4 to 6 hours, or as directed by a doctor

 do not take more than 6 doses in 24 hours

adults and children
12 years of age and over 1 to 2 capsules
children 6 to
under 12 years of age 1 capsule
children under 6 years of age do not use this product
in children under 6 years of age

OTHER INFORMATION

 store in a dry place at 15° – 30°C (59° – 86°F)

INACTIVE INGREDIENT

corn starch, D&C red #28, FD&C blue #1, FD&C red #40, gelatin, lactose monohydrate, magnesium stearate, sodium lauryl sulfate

KEEP OUT OF REACH OF CHILDREN. DO NOT USE IF PRODUCT APPEARS TO BE
TAMPERED WITH OR IMPRINTED SEAL UNDER CAP IS BROKEN OR MISSING.
DO NOT USE IF RED CAPSULE BAND IS BROKEN OR MISSING.

PREGNANCY OR BREAST FEEDING

If pregnant or breast-feeding, ask a health professional before use.

QUESTIONS OR COMMENTS

1-800-616-2471

When using this product

 marked drowsiness may occur

 avoid alcoholic drinks
 alcohol, sedatives and tranquilizers may increase drowsiness

 be careful when driving a motor vehicle or operating machinery

 excitability may occur, especially in children

DOSAGE AND ADMINISTRATION

ORAL

Diphenhydramine HCl 25 mg

take every 4 to 6 hours, or as directed by a doctor

do not take more than 6 doses in 24 hours

INDICATIONS AND USAGE

 temporarily relieves these symptoms due to hay fever or other upper respiratory allergies:  runny nose  sneezing  itchy, watery eyes  itching of the nose or throat